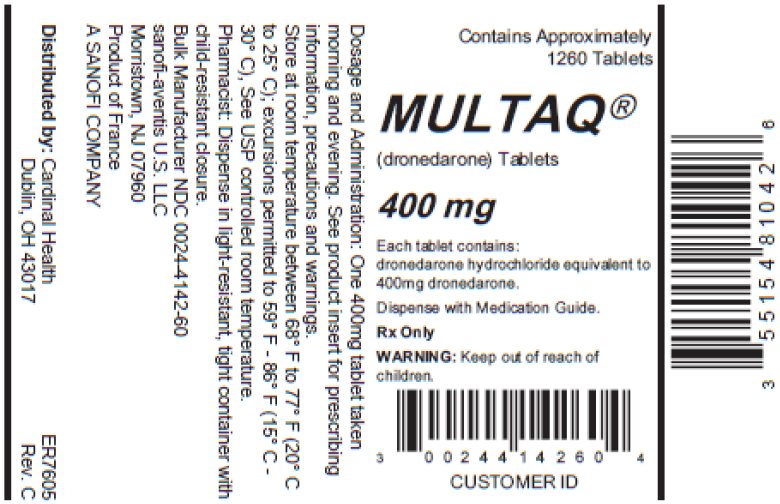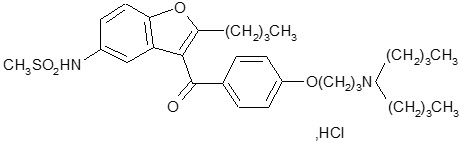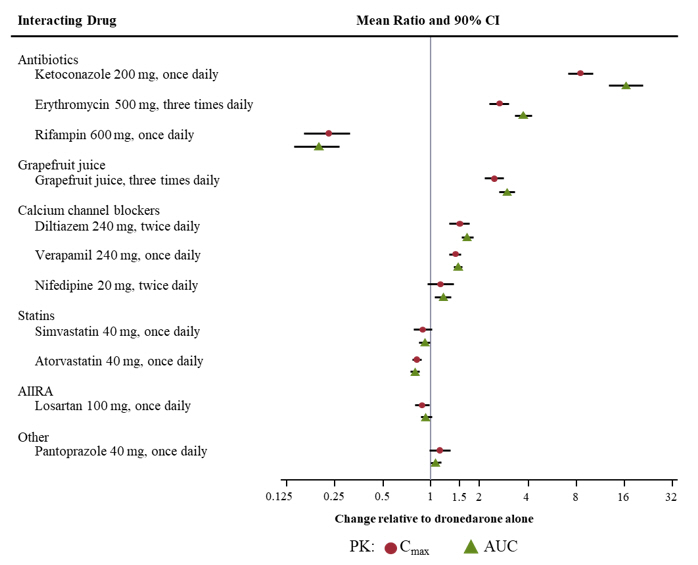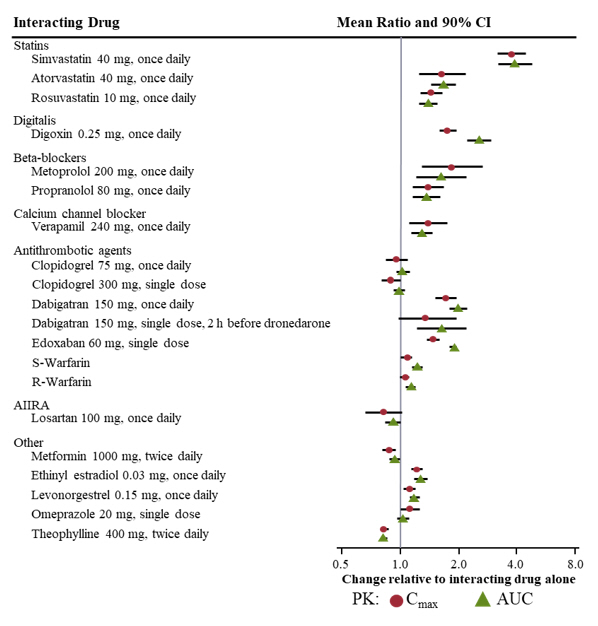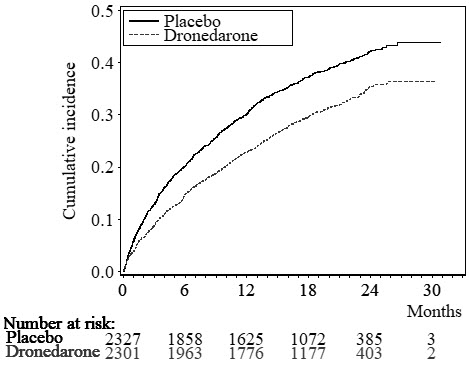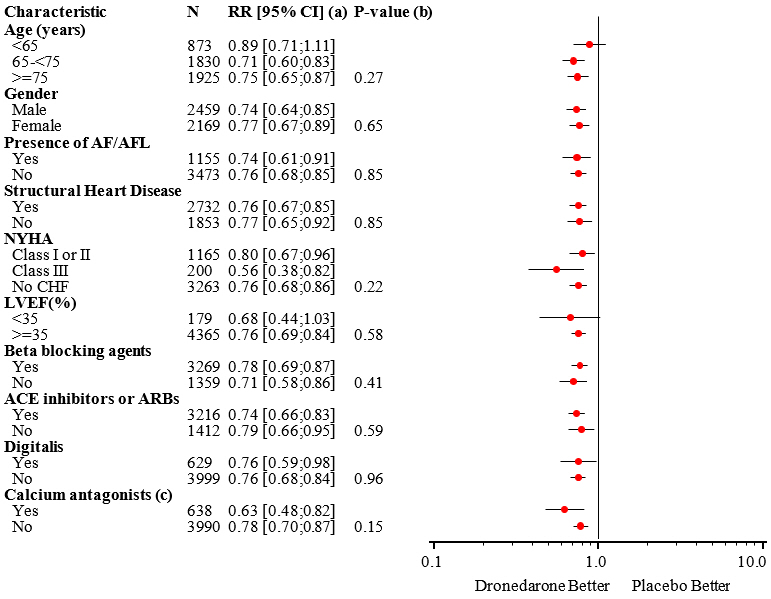 DRUG LABEL: Multaq
NDC: 55154-8104 | Form: TABLET, FILM COATED
Manufacturer: Cardinal Health 107, LLC
Category: prescription | Type: HUMAN PRESCRIPTION DRUG LABEL
Date: 20260127

ACTIVE INGREDIENTS: DRONEDARONE 400 mg/1 1
INACTIVE INGREDIENTS: SILICON DIOXIDE; CROSPOVIDONE (120 .MU.M); HYPROMELLOSE, UNSPECIFIED; LACTOSE MONOHYDRATE; MAGNESIUM STEARATE; POLOXAMER 407; STARCH, CORN; CARNAUBA WAX; POLYETHYLENE GLYCOL 6000; TITANIUM DIOXIDE

HIGHLIGHTS OF PRESCRIBING INFORMATION

These highlights do not include all the information needed to use MULTAQ safely and effectively. See full prescribing information for MULTAQ.
MULTAQ® (dronedarone) tablets, for oral use
Initial U.S. Approval: 2009

WARNING: INCREASED RISK OF DEATH, STROKE AND HEART FAILURE IN PATIENTS WITH DECOMPENSATED HEART FAILURE OR PERMANENT ATRIAL FIBRILLATION

See full prescribing information for complete boxed warning.

MULTAQ is contraindicated in patients with symptomatic heart failure with recent decompensation requiring hospitalization or NYHA Class IV heart failure. MULTAQ doubles the risk of death in these patients. (4, 5.1, 14.3)

MULTAQ is contraindicated in patients in atrial fibrillation (AF) who will not or cannot be cardioverted into normal sinus rhythm. In patients with permanent AF, MULTAQ doubles the risk of death, stroke, and hospitalization for heart failure. (4, 5.2, 14.4)

1 INDICATIONS AND USAGE

MULTAQ is an antiarrhythmic drug indicated to reduce the risk of hospitalization for atrial fibrillation (AF) in patients in sinus rhythm with a history of paroxysmal or persistent AF (1, 14).

2 DOSAGE AND ADMINISTRATION

One tablet of 400 mg twice a day with morning and evening meals (2)

3 DOSAGE FORMS AND STRENGTHS

400 mg film-coated tablets (3)

4 CONTRAINDICATIONS

- Permanent AF (patients in whom normal sinus rhythm will not or cannot be restored) (Boxed Warning, 4)
- Recently decompensated heart failure requiring hospitalization or Class IV heart failure (Boxed Warning, 4)
- Second or third-degree atrioventricular (AV) block or sick sinus syndrome (except when used in conjunction with a functioning pacemaker) (4)
- Bradycardia <50 bpm (4)
- Concomitant use of a strong CYP3A inhibitor (4)
- Concomitant use of erythromycin (4)
- Concomitant use of drugs or herbal products that prolong the QT interval and may induce torsade de pointes (4)
- Liver or lung toxicity related to the previous use of amiodarone (4)
- QTc interval >500 ms or PR interval >280 ms (4)
- Severe hepatic impairment (4)
- Hypersensitivity to the active substance or to any of the excipients (4)

5 WARNINGS AND PRECAUTIONS

- Determine cardiac rhythm at least once every 3 months. If AF is detected discontinue MULTAQ or cardiovert. (5.2)
- Ensure appropriate antithrombotic therapy prior to and throughout MULTAQ use. (5.3)
- Liver injury: If hepatic injury is suspected, discontinue MULTAQ. (5.5)
- If pulmonary toxicity is confirmed, discontinue treatment. (5.6)
- Hypokalemia and hypomagnesemia: Maintain potassium and magnesium levels within the normal range. (5.7)
- Renal impairment: Monitor renal function periodically. (5.9)
- Embryofetal Toxicity: Based on animal data, MULTAQ may cause fetal harm when administered to a pregnant woman. Advise females of reproductive potential of the potential risk to a fetus and to use effective contraception while using MULTAQ. (5.10)

6 ADVERSE REACTIONS

Most common adverse reactions (≥2%) are diarrhea, nausea, abdominal pain, vomiting, dyspepsia, bradycardia, skin issues (rashes, pruritus, eczema, dermatitis, dermatitis allergic), and asthenia (6)

To report SUSPECTED ADVERSE REACTIONS, contact sanofi-aventis U.S. LLC at 1-800-633-1610 or FDA at 1-800-FDA-1088 or www.fda.gov/medwatch.

7 DRUG INTERACTIONS

Dronedarone is metabolized by CYP3A and is a moderate inhibitor of CYP3A and CYP2D6 and has potentially important pharmacodynamic interactions (7)

- Class I or III antiarrhythmics: Contraindicated. (4, 7.1)
- Digoxin: Consider discontinuation or halve dose of digoxin before treatment and monitor digoxin levels. (7.1, 7.3)
- Calcium channel blockers (CCB): Initiate CCB with low dose and increase after ECG verification of tolerability. (7.1, 7.2, 7.3)
- Beta-blockers: May provoke excessive bradycardia. Initiate with low dose and increase after ECG verification of tolerability. (7.1, 7.3)
- CYP3A inducers: Avoid concomitant use. (7.2)
- Grapefruit juice: Avoid concomitant use. (7.2)
- Statins: Avoid simvastatin doses greater than 10 mg daily. Follow label recommendations for concomitant use of other statins with a CYP3A and P-gp inhibitor like dronedarone. (7.3)
- CYP3A substrates with a narrow therapeutic index (e.g., sirolimus and tacrolimus): Monitor and adjust dosage of concomitant drug as needed when used with MULTAQ. (7.3)
- Warfarin: Monitor INR after initiating dronedarone in patients taking warfarin. (7.3)

8 USE IN SPECIFIC POPULATIONS

- Lactation: Do not breastfeed (8.2)

FULL PRESCRIBING INFORMATION

WARNING: INCREASED RISK OF DEATH, STROKE AND HEART FAILURE IN PATIENTS WITH DECOMPENSATED HEART FAILURE OR PERMANENT ATRIAL FIBRILLATION

In patients with symptomatic heart failure and recent decompensation requiring hospitalization or NYHA Class IV heart failure, MULTAQ doubles the risk of death [see Clinical Studies (14.3)]. MULTAQ is contraindicated in patients with symptomatic heart failure with recent decompensation requiring hospitalization or NYHA Class IV heart failure [see Contraindications (4), Warnings and Precautions (5.1)].

In patients with permanent atrial fibrillation, MULTAQ doubles the risk of death, stroke and hospitalization for heart failure [see Clinical Studies (14.4)]. MULTAQ is contraindicated in patients in atrial fibrillation (AF) who will not or cannot be cardioverted into normal sinus rhythm [see Contraindications (4), Warnings and Precautions (5.2)].

1 INDICATIONS AND USAGE

MULTAQ® is indicated to reduce the risk of hospitalization for atrial fibrillation in patients in sinus rhythm with a history of paroxysmal or persistent atrial fibrillation (AF) [see Clinical Studies (14)].

2 DOSAGE AND ADMINISTRATION

The recommended dosage of MULTAQ is 400 mg twice daily in adults. MULTAQ should be taken as one tablet with the morning meal and one tablet with the evening meal.

Treatment with Class I or III antiarrhythmics (e.g., amiodarone, flecainide, propafenone, quinidine, disopyramide, dofetilide, sotalol) or drugs that are strong inhibitors of CYP3A (e.g., ketoconazole) must be stopped before starting MULTAQ [see Contraindications (4)].

Verify that females of reproductive potential are not pregnant prior to initiating MULTAQ [see Warnings and Precautions (5.10), Use in Specific Populations (8.1, 8.3)].

3 DOSAGE FORMS AND STRENGTHS

MULTAQ 400 mg tablets are provided as white film-coated tablets for oral administration, oblong-shaped, engraved with a double wave marking on one side and "4142" code on the other side.

4 CONTRAINDICATIONS

MULTAQ is contraindicated in patients with:

- Permanent atrial fibrillation (patients in whom normal sinus rhythm will not or cannot be restored) [see Boxed Warning, Warnings and Precautions (5.2)]
- Symptomatic heart failure with recent decompensation requiring hospitalization or NYHA Class IV symptoms [see Boxed Warning, Warnings and Precautions (5.1)]
- Second or third-degree atrioventricular (AV) block, or sick sinus syndrome (except when used in conjunction with a functioning pacemaker)
- Bradycardia <50 bpm
- Concomitant use of strong CYP3A inhibitors, such as ketoconazole, itraconazole, voriconazole, cyclosporine, telithromycin, clarithromycin, nefazodone, and ritonavir [see Drug Interactions (7.2)]
- Concomitant use of erythromycin [see Clinical Pharmacology (12.3)]
- Concomitant use of drugs or herbal products that prolong the QT interval and might increase the risk of torsade de pointes, such as phenothiazine antipsychotics, tricyclic antidepressants, certain oral macrolide antibiotics, and Class I and III antiarrhythmics
- Liver or lung toxicity related to the previous use of amiodarone
- QTc interval >500 ms or PR interval >280 ms
- Severe hepatic impairment
- Hypersensitivity to the active substance or to any of the excipients

5 WARNINGS AND PRECAUTIONS

5.1 Cardiovascular Death in NYHA Class IV or Decompensated Heart Failure

MULTAQ is contraindicated in patients with NYHA Class IV heart failure or symptomatic heart failure with recent decompensation requiring hospitalization because it doubles the risk of death.

5.2 Cardiovascular Death and Heart Failure in Permanent AF

MULTAQ doubles the risk of cardiovascular death (largely arrhythmic) and heart failure events in patients with permanent AF. Patients treated with dronedarone should undergo monitoring of cardiac rhythm no less often than every 3 months. Cardiovert patients who are in atrial fibrillation (if clinically indicated) or discontinue MULTAQ. MULTAQ offers no benefit in subjects in permanent AF.

5.3 Increased Risk of Stroke in Permanent AF

In a placebo-controlled study in patients with permanent atrial fibrillation, dronedarone was associated with an increased risk of stroke, particularly in the first two weeks of therapy [see Clinical Studies (14.4)]. MULTAQ should only be initiated in patients in sinus rhythm who are receiving appropriate antithrombotic therapy [see Drug Interactions (7.3)].

5.4 New Onset or Worsening Heart Failure

New onset or worsening of heart failure has been reported during treatment with MULTAQ in the postmarketing setting. In a placebo-controlled study in patients with permanent AF increased rates of heart failure were observed in patients with normal left ventricular function and no history of symptomatic heart failure, as well as those with a history of heart failure or left ventricular dysfunction.

Advise patients to consult a physician if they develop signs or symptoms of heart failure, such as weight gain, dependent edema, or increasing shortness of breath. If heart failure develops or worsens and requires hospitalization, discontinue MULTAQ.

5.5 Liver Injury

Hepatocellular liver injury, including acute liver failure requiring transplant, has been reported in patients treated with MULTAQ in the postmarketing setting. Advise patients treated with MULTAQ to report immediately symptoms suggesting hepatic injury (such as anorexia, nausea, vomiting, fever, malaise, fatigue, right upper quadrant pain, jaundice, dark urine, or itching). Consider obtaining periodic hepatic serum enzymes, especially during the first 6 months of treatment, but it is not known whether routine periodic monitoring of serum enzymes will prevent the development of severe liver injury. If hepatic injury is suspected, promptly discontinue MULTAQ and test serum enzymes, aspartate aminotransferase (AST), alanine aminotransferase (ALT) and alkaline phosphatase, as well as serum bilirubin, to establish whether there is liver injury. If liver injury is found, institute appropriate treatment and investigate the probable cause. Do not restart MULTAQ in patients without another explanation for the observed liver injury.

5.6 Pulmonary Toxicity

Cases of interstitial lung disease including pneumonitis and pulmonary fibrosis have been reported in patients treated with MULTAQ in the postmarketing setting [see Adverse Reactions (6.2)]. Onset of dyspnea or non-productive cough may be related to pulmonary toxicity and patients should be carefully evaluated clinically. If pulmonary toxicity is confirmed, MULTAQ should be discontinued.

5.7 Hypokalemia and Hypomagnesemia with Potassium-Depleting Diuretics

Hypokalemia or hypomagnesemia may occur with concomitant administration of potassium-depleting diuretics. Potassium levels should be within the normal range prior to administration of MULTAQ and maintained in the normal range during administration of MULTAQ.

5.8 QT Interval Prolongation

MULTAQ is associated with concentration-dependent QTcF interval prolongation (estimated QTcF increase for 400 mg BID with food is 15 ms) [see Clinical Pharmacology (12.2)]. If the QTc interval is >500 ms, discontinue MULTAQ [see Contraindications (4)].

5.9 Renal Impairment and Failure

Marked increase in serum creatinine, pre-renal azotemia and acute renal failure, often in the setting of heart failure [see Warnings and Precautions (5.4)] or hypovolemia, have been reported in patients taking MULTAQ. In most cases, these effects appear to be reversible upon drug discontinuation and with appropriate medical treatment. Monitor renal function periodically.

Small increases in creatinine levels (about 0.1 mg/dL) following dronedarone treatment initiation have been shown to be a result of inhibition of creatinine's tubular secretion. The elevation has a rapid onset, reaches a plateau after 7 days and is reversible after discontinuation.

5.10 Embryofetal Toxicity

Based on animal data, MULTAQ may cause fetal harm when administered to a pregnant woman. Dronedarone caused multiple visceral and skeletal malformations in animal reproduction studies when pregnant rats and rabbits were administered dronedarone at doses equivalent to recommended human doses. Advise pregnant women of the potential risk to the fetus. Verify that females of reproductive potential are not pregnant prior to initiating MULTAQ. Advise females of reproductive potential to use effective contraception during treatment with MULTAQ and for 5 days (about 6 half-lives) after the final dose [see Use in Specific Populations (8.1, 8.3)].

6 ADVERSE REACTIONS

The following safety concerns are described elsewhere in the label:

- New or worsening heart failure [see Warnings and Precautions (5.4)]
- Liver Injury [see Warnings and Precautions (5.5)]
- Pulmonary toxicity [see Warnings and Precautions (5.6)]
- Hypokalemia and hypomagnesemia with potassium-depleting diuretics [see Warnings and Precautions (5.7)]
- QT prolongation [see Warnings and Precautions (5.8)]

6.1 Clinical Trials Experience

The safety evaluation of dronedarone 400 mg twice daily in patients with AF or AFL is based on 5 placebo-controlled studies, ATHENA, EURIDIS, ADONIS, ERATO and DAFNE. In these studies, a total of 6285 patients were randomized and treated, 3282 patients with MULTAQ 400 mg twice daily, and 2875 with placebo. The mean exposure across studies was 12 months. In ATHENA, the maximum follow-up was 30 months.

In clinical trials, premature discontinuation because of adverse reactions occurred in 11.8% of the dronedarone-treated patients and in 7.7% of the placebo-treated group. The most common reasons for discontinuation of therapy with MULTAQ were gastrointestinal disorders (3.2% vs 1.8% in the placebo group) and QT prolongation (1.5% vs 0.5% in the placebo group).

The most frequent adverse reactions observed with MULTAQ 400 mg twice daily in the 5 studies were diarrhea, nausea, abdominal pain, vomiting, and asthenia.

Table 1 displays adverse reactions more common with dronedarone 400 mg twice daily than with placebo in AF or AFL patients, presented by system organ class and by decreasing order of frequency. Adverse laboratory and ECG effects are presented separately in Table 2.

Table 1: Adverse Drug Reactions that Occurred in at Least 1% of Patients and were More Frequent than Placebo
 | Placebo | Dronedarone 400 mg twice daily
 | (N=2875) | (N=3282)
Gastrointestinal
Diarrhea | 6% | 9%
Nausea | 3% | 5%
Abdominal pain | 3% | 4%
Vomiting | 1% | 2%
Dyspeptic signs and symptoms | 1% | 2%
General
Asthenic conditions | 5% | 7%
Cardiac
Bradycardia | 1% | 3%
Skin and subcutaneous tissue
Including rashes (generalized, macular, maculo-papular, erythematous), pruritus, eczema, dermatitis, dermatitis allergic | 3% | 5%

Photosensitivity reaction and dysgeusia have also been reported at an incidence less than 1% in patients treated with MULTAQ.

The following laboratory data/ECG parameters were reported with MULTAQ 400 mg twice daily.

Table 2: Laboratory Data/ECG Parameters Not Necessarily Reported as Adverse Events
 | Placebo | MULTAQ 400 mg twice daily
 | (N=2875) | (N=3282)
Early increases in creatinine ≥10% | 21% | 51%
 | (N=2237) | (N=2701)
QTc prolonged | 19% | 28%

Assessment of demographic factors such as gender or age on the incidence of treatment-emergent adverse events did not suggest an excess of adverse events in any particular subgroup.

In randomized clinical trials of patients with paroxysmal or persistent atrial fibrillation, one case of torsade de pointes was reported in patients treated with MULTAQ (2301 patients) versus no cases of torsade de pointes in patients treated with placebo (2327) in the ATHENA study. No cases of torsade de pointes were reported in patients treated with MULTAQ (828 patients) or placebo (409 patients) in the EURIDIS and ADONIS studies [see Clinical Studies (14)].

6.2 Postmarketing Experience

The following adverse reactions have been identified during postapproval use of MULTAQ. Because these reactions are reported voluntarily from a population of an unknown size, it is not always possible to reliably estimate their frequency or establish a causal relationship to drug exposure.

Cardiac: New or worsening heart failure [see Warnings and Precautions (5.4)]

Atrial flutter with 1:1 atrioventricular conduction has been reported very rarely.

Hepatic: Liver injury [see Warnings and Precautions (5.5)]

Respiratory: Interstitial lung disease including pneumonitis and pulmonary fibrosis [see Warnings and Precautions (5.6)]

Immune: Anaphylactic reactions including angioedema

Vascular: Vasculitis, including leukocytoclastic vasculitis

7 DRUG INTERACTIONS

7.1 Pharmacodynamic Interactions

Drugs Prolonging the QT Interval (Inducing Torsade de Pointes)

Coadministration of drugs prolonging the QT interval (such as certain phenothiazines, tricyclic antidepressants, certain macrolide antibiotics, and Class I and III antiarrhythmics) is contraindicated because of the potential risk of torsade de pointes–type ventricular tachycardia [see Contraindications (4), Clinical Pharmacology (12.3)].

Digoxin

In the ANDROMEDA (patients with recently decompensated heart failure) and PALLAS (patients with permanent AF) trials baseline use of digoxin was associated with an increased risk of arrhythmic or sudden death in dronedarone-treated patients compared to placebo. In patients not taking digoxin, no difference in risk of sudden death was observed in the dronedarone versus placebo groups [see Clinical Studies (14.3)].

Digoxin can potentiate the electrophysiologic effects of dronedarone (such as decreased AV-node conduction). Dronedarone increases exposure to digoxin [see Drug Interactions (7.3), Clinical Pharmacology (12.3)].

Consider discontinuing digoxin. If digoxin treatment is continued, halve the dose of digoxin, monitor serum levels closely, and observe for toxicity.

Calcium Channel Blockers

Calcium channel blockers with depressant effects on the sinus and AV nodes could potentiate dronedarone's effects on conduction.

Give a low dose of calcium channel blockers initially and increase only after ECG verification of good tolerability [see Drug Interactions (7.3), Clinical Pharmacology (12.3)].

Beta-Blockers

In clinical trials, bradycardia was more frequently observed when dronedarone was given in combination with beta-blockers.

Give a low dose of beta-blockers initially, and increase only after ECG verification of good tolerability [see Drug Interactions (7.3), Clinical Pharmacology (12.3)].

7.2 Effects of Other Drugs on Dronedarone

Ketoconazole and Other Potent CYP3A Inhibitors

Concomitant use of ketoconazole as well as other potent CYP3A inhibitors such as itraconazole, voriconazole, ritonavir, clarithromycin, and nefazodone is contraindicated because exposure to dronedarone is significantly increased [see Contraindications (4), Clinical Pharmacology (12.3)].

Grapefruit Juice

Patients should avoid grapefruit juice beverages while taking MULTAQ because exposure to dronedarone is significantly increased [see Clinical Pharmacology (12.3)].

Rifampin and Other CYP3A Inducers

Avoid rifampin or other CYP3A inducers such as phenobarbital, carbamazepine, phenytoin, and St. John's wort because they decrease exposure to dronedarone significantly [see Clinical Pharmacology (12.3)].

Calcium Channel Blockers

Verapamil and diltiazem are moderate CYP3A inhibitors and increase dronedarone exposure. Give a low dose of calcium channel blockers initially and increase only after ECG verification of good tolerability [see Drug Interactions (7.3), Clinical Pharmacology (12.3)].

7.3 Effects of Dronedarone on Other Drugs

Simvastatin

Dronedarone increased simvastatin/simvastatin acid exposure. Avoid doses greater than 10 mg once daily of simvastatin [see Clinical Pharmacology (12.3)].

Other Statins

Because of multiple mechanisms of interaction with statins (CYPs and transporters), follow statin label recommendations for use with CYP3A and P-gp inhibitors such as dronedarone.

Calcium Channel Blockers

Dronedarone increased the exposure of calcium channel blockers (verapamil, diltiazem or nifedipine). Give a low dose of calcium channel blockers initially and increase only after ECG verification of good tolerability [see Drug Interactions (7.1), Clinical Pharmacology (12.3)].

Sirolimus, Tacrolimus, and Other CYP3A Substrates with Narrow Therapeutic Range

Dronedarone can increase plasma concentrations of tacrolimus, sirolimus, and other CYP3A substrates with a narrow therapeutic range when given orally. Monitor plasma concentrations and adjust dosage appropriately.

Beta-Blockers and Other CYP2D6 Substrates

Dronedarone increased the exposure of propranolol and metoprolol. Give low doses of beta-blockers initially, and increase only after ECG verification of good tolerability. Other CYP2D6 substrates, including other beta-blockers, tricyclic antidepressants, and selective serotonin reuptake inhibitors (SSRIs) may have increased exposure upon coadministration with dronedarone [see Drug Interactions (7.1), Clinical Pharmacology (12.3)].

P-glycoprotein Substrates

Digoxin

Dronedarone increased digoxin exposure by inhibiting the P-gp transporter. Consider discontinuing digoxin. If digoxin treatment is continued, halve the dose of digoxin, monitor serum levels closely, and observe for toxicity [see Drug Interactions (7.1), Clinical Pharmacology (12.3)].

Dabigatran

Dronedarone increases dabigatran plasma exposures by inhibiting the P-gp transporter [see Clinical Pharmacology (12.3)]. In patients with moderate renal impairment (CrCL 30–50 mL/min), reduce the dose of dabigatran to 75 mg twice daily when concomitantly administered with dronedarone. In patients with severe renal impairment (CrCL 15–30 mL/min), concomitant use of dronedarone with dabigatran should be avoided.

Warfarin

When coadministered with dronedarone exposure to S-warfarin was slightly higher than when warfarin was administered alone. There were no clinically significant increases in INR [see Clinical Pharmacology (12.3)].

More patients experienced clinically significant INR elevations (≥5) usually within 1 week after starting dronedarone versus placebo in patients taking oral anticoagulants in ATHENA. However, no excess risk of bleeding was observed in the dronedarone group.

Postmarketing cases of increased INR with or without bleeding events have been reported in warfarin-treated patients initiated on dronedarone. Monitor INR after initiating dronedarone in patients taking warfarin.

8 USE IN SPECIFIC POPULATIONS

8.1 Pregnancy

TERATOGENIC EFFECTS

Risk Summary

MULTAQ may cause fetal harm when administered to a pregnant woman. In animal studies, dronedarone administered to pregnant rats and rabbits during the period of organogenesis caused multiple visceral (rats) and skeletal malformations (rats and rabbits) when administered at doses equivalent to or lower than the maximum recommended human dose (MRHD) (see Data). There are no available data on dronedarone use in pregnant women to evaluate for a drug-associated risk of major birth defects or miscarriage or other adverse maternal or fetal outcomes. Advise pregnant women of the potential risk to a fetus. The background risk of major birth defects and miscarriage for the indicated population is unknown. All pregnancies have a background risk of birth defect, loss, or other adverse outcomes. In the U.S. general population, the estimated background risk of major birth defects and miscarriage in clinically recognized pregnancies is 2% to 4% and 15% to 20%, respectively.

Data

Animal data

When pregnant rats in embryofetal development studies received dronedarone at oral doses greater than or equal to the MRHD (on a mg/m^2 basis) during organogenesis (gestational days 6 to 15) fetuses had increased rates of external, visceral and skeletal malformations (cranioschisis, cleft palate, incomplete evagination of pineal body, brachygnathia, partially fused carotid arteries, truncus arteriosus, abnormal lobation of the liver, partially duplicated inferior vena cava, brachydactyly, ectrodactyly, syndactyly, and anterior and/or posterior club feet). When pregnant rabbits in embryofetal development studies received dronedarone, at a dose approximately half the MRHD (on a mg/m^2 basis) during organogenesis (gestational days 6 to 18), fetuses had an increased rate of skeletal abnormalities (anomalous ribcage and vertebrae, pelvic asymmetry) at doses ≥20 mg/kg (the lowest dose tested and approximately half the MRHD on a mg/m^2 basis).

Actual animal doses: rat (≥80 mg/kg/day); rabbit (≥20 mg/kg)

8.2 Lactation

Risk Summary

There are no available data on the presence of dronedarone in human milk, the effects on the breastfed infant, or the effect on milk production. Dronedarone and its metabolites are present in rat milk. During a prenatal and postnatal study in rats, maternal dronedarone administration was associated with minor reduced body-weight gain in the offspring. When a drug is present in animal milk, it is likely that the drug will be present in human milk. Because of the potential for serious adverse reactions in breastfed infants from MULTAQ like the adverse effects in adults, (liver injury, and pulmonary toxicity), advise patients not to breastfeed during treatment with MULTAQ and for 5 days (about 6 half-lives) after the last dose.

8.3 Females and Males of Reproductive Potential

MULTAQ may cause fetal harm when administered to pregnant women [see Use in Specific Populations (8.1)].

Pregnancy Testing

Verify that females of reproductive potential are not pregnant prior to initiating MULTAQ.

Contraception

Advise female patients of reproductive potential to use effective contraception during treatment with MULTAQ and for 5 days after the final dose.

8.4 Pediatric Use

Safety and efficacy in children below the age of 18 years have not been established.

8.5 Geriatric Use

More than 4500 patients with AF or AFL aged 65 years or above were included in the MULTAQ clinical program (of whom more than 2000 patients were 75 years or older). Efficacy and safety were similar in elderly and younger patients.

8.6 Renal Impairment

Patients with renal impairment were included in clinical studies. Because renal excretion of dronedarone is minimal [see Clinical Pharmacology (12.3)], no dosing alteration is needed.

8.7 Hepatic Impairment

Dronedarone is extensively metabolized by the liver. There is little clinical experience with moderate hepatic impairment and none with severe impairment. No dosage adjustment is recommended for moderate hepatic impairment [see Contraindications (4), Clinical Pharmacology (12.3)].

10 OVERDOSAGE

In the event of overdosage, monitor the patient's cardiac rhythm and blood pressure. Treatment should be supportive and based on symptoms.

It is not known whether dronedarone or its metabolites can be removed by dialysis (hemodialysis, peritoneal dialysis or hemofiltration). There is no specific antidote available.

11 DESCRIPTION

Dronedarone HCl is a benzofuran derivative with the following chemical name:

N-{2-butyl-3-[4-(3-dibutylaminopropoxy)benzoyl]benzofuran-5-yl} methanesulfonamide, hydrochloride.

Dronedarone HCl is a white fine powder that is practically insoluble in water and freely soluble in methylene chloride and methanol.

Its empirical formula is C31H44N2O5 S, HCl with a relative molecular mass of 593.2. Its structural formula is:

MULTAQ is provided as tablets for oral administration.

Each tablet of MULTAQ contains 400 mg of dronedarone (expressed as base).

The inactive ingredients are:

Core of the tablets: Colloidal silicon dioxide, crospovidone, hypromellose, lactose monohydrate, magnesium stearate, poloxamer 407, starch.
Coating/polishing of the tablets: Carnauba wax, hypromellose, polyethylene glycol 6000, titanium dioxide.

12 CLINICAL PHARMACOLOGY

12.1 Mechanism of Action

The mechanism of action of dronedarone is unknown. Dronedarone has antiarrhythmic properties belonging to all four Vaughan-Williams classes, but the contribution of each of these activities to the clinical effect is unknown.

12.2 Pharmacodynamics

Electrophysiological Effects

The effect of dronedarone on 12-lead ECG parameters was investigated in healthy subjects following repeated oral doses up to 1600 mg twice daily for 10 days. Concentration-dependent increases in QTcF and PR were observed and the estimated increases for 400 mg BID with food are 15 and 12 ms, respectively. The contribution of dronedarone and the N-debutyl metabolite to observed changes is unknown.

DAFNE Study

DAFNE was a dose-response study in patients with recurrent AF, evaluating the effect of dronedarone in comparison with placebo in maintaining sinus rhythm. The doses of dronedarone in this study were 400, 600, and 800 mg twice a day. In this small study, doses above 400 mg were not more effective and were less well tolerated.

12.3 Pharmacokinetics

Dronedarone is extensively metabolized and has low systemic bioavailability; its bioavailability is increased by meals. Its elimination half-life is 13 to 19 hours.

Absorption

Because of presystemic first pass metabolism the absolute bioavailability of dronedarone without food is low, about 4%. It increases to approximately 15% when dronedarone is administered with a high fat meal. After oral administration in fed conditions, peak plasma concentrations of dronedarone and the main circulating active metabolite (N-debutyl metabolite) are reached within 3 to 6 hours. After repeated administration of 400 mg twice daily, steady state is reached within 4 to 8 days of treatment and the mean accumulation ratio for dronedarone ranges from 2.6 to 4.5. The steady-state Cmax and exposure of the main N-debutyl metabolite is similar to that of the parent compound. The pharmacokinetics of dronedarone and its N-debutyl metabolite both deviate moderately from dose proportionality: a doubling in dose results in approximately 2.5 to 3.0-fold the Cmax and AUC.

Distribution

The in vitro plasma protein binding of dronedarone and its N-debutyl metabolite is >98% and not saturable. Both compounds bind mainly to albumin. After intravenous (IV) administration the volume of distribution at steady state is about 1400 L.

Metabolism

Dronedarone is extensively metabolized, mainly by CYP3A. The initial metabolic pathway includes N-debutylation to form the active N-debutyl metabolite, oxidative deamination to form the inactive propanoic acid metabolite, and direct oxidation. The metabolites undergo further metabolism to yield over 30 uncharacterized metabolites. Monoamine oxidases contribute partially to the metabolism of the active metabolite of dronedarone.

Excretion/Elimination

In a mass balance study with orally administered dronedarone (^14C-labeled) approximately 6% of the labeled dose was excreted in urine, mainly as metabolites (no unchanged compound excreted in urine), and 84% was excreted in feces, mainly as metabolites. Dronedarone and its N-debutyl active metabolite accounted for less than 15% of the resultant radioactivity in the plasma.

After IV administration the plasma clearance of dronedarone ranges from 130 to 150 L/h. The elimination half-life of dronedarone ranges from 13 to 19 hours.

Special Populations

Gender

Dronedarone exposures are on average 30% higher in females than in males.

Race

Pharmacokinetic differences related to race were not formally assessed. However, based on a cross study comparison, following single dose administration (400 mg), Asian males (Japanese) have about twice the exposure than Caucasian males. The pharmacokinetics of dronedarone in other races has not been assessed.

Elderly

Of the total number of subjects in clinical studies of dronedarone, 73% were 65 years of age and over and 34% were 75 and over. In patients aged 65 years old and above, dronedarone exposures are 23% higher than in patients less than 65 years old [see Use in Specific Populations (8.5)].

Hepatic impairment

In subjects with moderate hepatic impairment, the mean dronedarone exposure increased by 30% relative to subjects with normal hepatic function and the mean exposure of the N-debutyl metabolite decreased by about 50%. Pharmacokinetic data were significantly more variable in subjects with moderate hepatic impairment.

The effect of severe hepatic impairment on the pharmacokinetics of dronedarone was not assessed [see Contraindications (4)].

Renal impairment

Consistent with the low renal excretion of dronedarone, no pharmacokinetic difference was observed in subjects with mild or moderate renal impairment compared to subjects with normal renal function [see Use in Specific Populations (8.6)]. No pharmacokinetic difference was observed in patients with mild to severe renal impairment in comparison with patients with normal renal function.

Drug Interactions

Dronedarone is metabolized primarily by CYP3A and is a moderate inhibitor of CYP3A and CYP2D6. Dronedarone has no significant potential to inhibit CYP1A2, CYP2C9, CYP2C19, CYP2C8 and CYP2B6. It has the potential to inhibit P-glycoprotein (P-gp) transport. Dronedarone inhibits in vivo the tubular secretion of creatinine a substrate of the organic cation transporter (OCT2) [see Warnings and Precautions (5.9)].

In vitro dronedarone and the metabolites SR35021 and SR90154 show no significant potential to inhibit the organic anion transporters OAT1 and OAT3 or the organic cation transporter OCT1. However, in vitro data indicate that SR90154 is likely to inhibit the organic anion transporting polypeptides (OATP1B1, OATP1B3) in vivo.

Pharmacokinetic measures indicating the magnitude of these interactions are presented in Figure 1 (impact of coadministered drugs on dronedarone) and Figure 2 (impact of dronedarone on coadministered drugs).

Figure 1: The Impact of Coadministered Drugs on the Pharmacokinetics of Dronedarone and Recommendations for Dronedarone Coadministration or Dose Adjustment

Figure 2: The Impact of Dronedarone on Coadministered Drugs and Recommendations for Dose Adjustment of Coadministered Drug

13 NONCLINICAL TOXICOLOGY

13.1 Carcinogenesis, Mutagenesis, Impairment of Fertility

In studies in which dronedarone was administered to rats and mice for up to 2 years at doses of up to 70 mg/kg/day and 300 mg/kg/day, respectively, there was an increased incidence of histiocytic sarcomas in dronedarone-treated male mice (300 mg/kg/day or 5 × the maximum recommended human dose based on AUC comparisons), mammary adenocarcinomas in dronedarone-treated female mice (300 mg/kg/day or 8 × MRHD based on AUC comparisons) and hemangiomas in dronedarone-treated male rats (70 mg/kg/day or 5 × MRHD based on AUC comparisons).

Dronedarone did not demonstrate genotoxic potential in the in vivo mouse micronucleus test, the Ames bacterial mutation assay, the unscheduled DNA synthesis assay, or an in vitro chromosomal aberration assay in human lymphocytes. S-9 processed dronedarone, however, was positive in a V79 transfected Chinese hamster V79 assay.

In fertility studies conducted with female rats, dronedarone given prior to breeding and implantation caused an increase in irregular estrus cycles and cessation of cycling at doses ≥10 mg/kg (equivalent to 0.12 × the MRHD on a mg/m^2 basis).

Corpora lutea, implantations and live fetuses were decreased at 100 mg/kg (equivalent to 1.2 × the MRHD on a mg/m^2 basis). There were no reported effects on mating behavior or fertility of male rats at doses of up to 100 mg/kg/day.

13.3 Developmental Toxicity

Dronedarone was teratogenic in rats given oral doses ≥80 mg/kg/day (a dose equivalent to the MRHD on a mg/m^2 basis), with fetuses showing external, visceral and skeletal malformations (cranioschisis, cleft palate, incomplete evagination of pineal body, brachygnathia, partially fused carotid arteries, truncus arteriosus, abnormal lobation of the liver, partially duplicated inferior vena cava, brachydactyly, ectrodactyly, syndactyly, and anterior and/or posterior club feet). In rabbits, dronedarone caused an increase in skeletal abnormalities (anomalous ribcage and vertebrae, pelvic asymmetry) at doses ≥20 mg/kg (the lowest dose tested and approximately half the MRHD on a mg/m^2 basis).

14 CLINICAL STUDIES

14.1 ATHENA

ATHENA was a multicenter, multinational, double blind, and randomized placebo-controlled study of dronedarone in 4628 patients with a recent history of AF/AFL who were in sinus rhythm or who were to be converted to sinus rhythm. The objective of the study was to determine whether dronedarone could delay death from any cause or hospitalization for cardiovascular reasons.

Initially patients were to be ≥70 years old, or <70 years old with at least one risk factor (including hypertension, diabetes, prior cerebrovascular accident, left atrial diameter ≥50 mm or LVEF <0.40). The inclusion criteria were later changed such that patients were to be ≥75 years old, or ≥70 years old with at least one risk factor. Patients had to have both AF/AFL and sinus rhythm documented within the previous 6 months. Patients could have been in AF/AFL or in sinus rhythm at the time of randomization, but patients not in sinus rhythm were expected to be either electrically or chemically converted to normal sinus rhythm after anticoagulation.

Subjects were randomized and treated for up to 30 months (median follow-up: 22 months) with either MULTAQ 400 mg twice daily (2301 patients) or placebo (2327 patients), in addition to conventional therapy for cardiovascular diseases that included beta-blockers (71%), ACE inhibitors or angiotensin II receptor blockers (ARBs) (69%), digoxin (14%), calcium antagonists (14%), statins (39%), oral anticoagulants (60%), aspirin (44%), other chronic antiplatelet therapy (6%) and diuretics (54%).

The primary endpoint of the study was the time to first hospitalization for cardiovascular reasons or death from any cause. Time to death from any cause, time to first hospitalization for cardiovascular reasons, and time to cardiovascular death and time to all causes of death were also explored.

Patients ranged in age from 23 to 97 years; 42% were 75 years old or older. Forty-seven percent (47%) of patients were female and a majority was Caucasian (89%). Seventy-one percent (71%) of those enrolled had no history of heart failure. The median ejection fraction was 60%. Twenty-nine percent (29%) of patients had heart failure, mostly NYHA class II (17%). The majority had hypertension (86%) and structural heart disease (60%).

Results are shown in Table 3. MULTAQ reduced the combined endpoint of cardiovascular hospitalization or death from any cause by 24.2% when compared to placebo. This difference was entirely attributable to its effect on cardiovascular hospitalization, principally hospitalization related to AF.

Other endpoints, death from any cause and first hospitalization for cardiovascular reasons, are shown in Table 3. Secondary endpoints count all first events of a particular type, whether or not they were preceded by a different type of event.

Table 3: Incidence of Endpoint Events
 | Placebo | MULTAQ 400 mg BID
 | (N=2327) | (N=2301) | HR | 95% CI | p-Value
Primary endpoint
Cardiovascular hospitalization or death from any cause | 913 (39.2%) | 727 (31.6%) | 0.76 | [0.68–0.83] | <0.0001
Components of the endpoint (as first event)
- Cardiovascular hospitalization | 856 (36.8%) | 669 (29.1%)
- Death from any cause | 57 (2.4%) | 58 (2.5%)
Secondary endpoints (any time in study)
- Death from any cause | 135 (5.8%) | 115 (5.0%) | 0.86 | [0.67–1.11] | 0.24
- Cardiovascular hospitalization | 856 (36.8%) | 669 (29.1%) | 0.74 | [0.67–0.82] | <0.0001
Components of the cardiovascular hospitalization endpoint (as first event)
- AF and other supraventricular rhythm disorders | 456 (19.6%) | 292 (12.7%) | 0.61 | [0.53–0.71] | <0.0001
- Other | 400 (17.2%) | 377 (16.4%) | 0.89 | [0.77–1.03] | 0.11

The Kaplan-Meier cumulative incidence curves showing the time to first event are displayed in Figure 3. The event curves separated early and continued to diverge over the 30-month follow-up period.

Figure 3: Kaplan-Meier Cumulative Incidence Curves from Randomization to First Cardiovascular Hospitalization or Death from Any Cause

Reasons for hospitalization included major bleeding (1% in both groups), syncope (1% in both groups), and ventricular arrhythmia (<1% in both groups).

The reduction in cardiovascular hospitalization or death from any cause was generally consistent in all subgroups based on baseline characteristics or medications (ACE inhibitors or ARBs; beta-blockers, digoxin, statins, calcium channel blockers, diuretics) (see Figure 4).

Figure 4: Relative Risk (MULTAQ vs Placebo) Estimates with 95% Confidence Intervals According to Selected Baseline Characteristics: First Cardiovascular Hospitalization or Death from Any Cause

(a) Determined from Cox regression model
(b) P-value of interaction between baseline characteristics and treatment based on Cox regression model
(c) Calcium antagonists with heart rate lowering effects restricted to diltiazem, verapamil and bepridil

14.2 EURIDIS and ADONIS

In EURIDIS and ADONIS, a total of 1237 patients in sinus rhythm with a prior episode of AF or AFL were randomized in an outpatient setting and treated with either MULTAQ 400 mg twice daily (n=828) or placebo (n=409) on top of conventional therapies (including oral anticoagulants, beta-blockers, ACE inhibitors or ARBs, chronic antiplatelet agents, diuretics, statins, digoxin, and calcium channel blockers). Patients had at least one ECG-documented AF/AFL episode during the 3 months prior to study entry but were in sinus rhythm for at least one hour. Patients ranged in age from 20 to 88 years, with the majority being Caucasian (97%), male (70%) patients. The most common comorbidities were hypertension (56.8%) and structural heart disease (41.5%), including coronary heart disease (21.8%). Patients were followed for 12 months.

In the pooled data from EURIDIS and ADONIS as well as in the individual trials, dronedarone delayed the time to first recurrence of AF/AFL (primary endpoint), lowering the risk of first AF/AFL recurrence during the 12-month study period by about 25%, with an absolute difference in recurrence rate of about 11% at 12 months.

14.3 ANDROMEDA

Patients recently hospitalized with symptomatic heart failure and severe left ventricular systolic dysfunction (wall motion index ≤1.2) were randomized to either MULTAQ 400 mg twice daily or matching placebo, with a primary composite end point of all-cause mortality or hospitalization for heart failure. Patients enrolled in ANDROMEDA were predominantly NYHA Class II (40%) and III (57%), and only 25% had AF at randomization. After enrollment of 627 patients and a median follow-up of 63 days, the trial was terminated because of excess mortality in the dronedarone group. Twenty-five (25) patients in the dronedarone group died versus 12 patients in the placebo group (hazard ratio 2.13; 95% CI: 1.07 to 4.25). The main reason for death was worsening heart failure. Baseline digoxin therapy was reported in 6/16 dronedarone patients versus 1/16 placebo patients who died of arrhythmia. In patients without baseline use of digoxin, no excess risk of arrhythmic death was observed in the dronedarone versus placebo groups.

There were also excess hospitalizations for cardiovascular reasons in the dronedarone group (71 vs 51 for placebo) [see Boxed Warning, Contraindications (4)].

14.4 PALLAS

Patients with permanent AF (AF documented in 2 weeks prior to randomization and at least 6 months prior to randomization in whom cardioversion had failed or was not planned) and additional risk factors for thromboembolism (coronary artery disease, prior stroke or TIA, symptomatic heart failure, LVEF <40%, peripheral arterial occlusive disease, or age >75 with hypertension and diabetes) were randomized to dronedarone 400 mg twice daily or placebo.

After enrollment of 3236 patients (placebo=1617 and dronedarone=1619) and a median follow up of 3.7 months for placebo and 3.9 for dronedarone, the study was terminated because of a significant increase in:

- Mortality: 25 dronedarone versus 13 placebo (HR, 1.94; CI: 0.99 to 3.79). The majority of deaths in the dronedarone group were classified as arrhythmic/sudden deaths (HR, 3.26; CI: 1.06 to 10.0). Baseline digoxin therapy was reported in 11/13 dronedarone patients who died of arrhythmia. None of the arrhythmic deaths on placebo (4) reported use of digoxin. In patients without baseline use of digoxin, no excess risk of arrhythmic death was observed in the dronedarone versus placebo groups.
- Stroke: 23 dronedarone versus 10 placebo (HR, 2.32; CI: 1.11 to 4.88). The increased risk of stroke observed with dronedarone was observed in the first two weeks of therapy (10 dronedarone vs 1 placebo), most of the subjects treated with dronedarone did not have an INR of 2.0 to 3.0 [see Warnings and Precautions (5.3)].
- Hospitalizations for heart failure in the dronedarone group: 43 dronedarone versus 24 placebo (HR, 1.81; CI: 1.10 to 2.99).

16 HOW SUPPLIED/STORAGE AND HANDLING

MULTAQ 400-mg tablets are provided as white film-coated tablets for oral administration, oblong-shaped, engraved with a double wave marking on one side and "4142" code on the other side in:

Bottles of approximately 1260 film-coated tablets, NDC 55154-8104-2

STORAGE AND HANDLING

Store at room temperature between 68°F to 77°F (20°C to 25°C): excursions permitted to 59°F–86°F (15°C–30°C), [see USP controlled room temperature].

17 PATIENT COUNSELING INFORMATION

Advise the patient to read the FDA-approved patient labeling (Medication Guide).

Administration Instructions

MULTAQ should be administered with a meal. Warn patients not to take MULTAQ with grapefruit juice.

If a dose is missed, patients should take the next dose at the regularly scheduled time and should not double the dose.

Advise patients to consult a physician before stopping treatment with MULTAQ.

New Onset or Worsening Heart Failure

Advise patients to consult a physician if they develop signs or symptoms of heart failure such as acute weight gain, dependent edema, or increasing shortness of breath.

Advise patients to inform their physician of any history of heart failure, rhythm disturbance other than atrial fibrillation or flutter or predisposing conditions such as uncorrected hypokalemia.

Liver Injury

Advise patients to immediately report any symptoms of potential liver injury (such as anorexia, nausea, vomiting, fever, malaise, fatigue, right upper quadrant abdominal discomfort, jaundice, dark urine, or itching) to their physician.

Drug Interactions

MULTAQ may interact with some drugs; therefore, advise patients to report to their doctor the use of any other prescription, non-prescription medication or herbal products, particularly St. John's wort.

Embryo-fetal Toxicity

MULTAQ may cause fetal harm. Advise female patients of reproductive potential to use effective contraception during treatment with MULTAQ and for 5 days after the final dose [see Use in Specific Populations (8.3)]. Advise females to inform their healthcare provider of a known or suspected pregnancy [see Warnings and Precautions (5.10) and Use in Specific Populations (8.1)].

Advise females not to breastfeed during treatment with MULTAQ and for 5 days after the final dose [see Use in Specific Populations (8.2)].

Manufactured by:

sanofi-aventis U.S. LLC
Morristown, NJ 07960
A SANOFI COMPANY

© sanofi-aventis 2025
All rights reserved.

MULTAQ is a registered trademark of sanofi-aventis.

Distributed By:

Cardinal Health

Dublin, OH 43017

ER7605 Rev. C

Medication Guide

MULTAQ® (MUL-tak)
(dronedarone)
tablets

What is the most important information I should know about MULTAQ?
MULTAQ may cause serious side effects, including:

- Increased risk of death, stroke, and heart failure in people with:
  - A certain type of heart failure called decompensated heart failure. Heart failure is when your heart does not pump blood through your body as well as it should. MULTAQ can cause new or worsening heart failure.
    Do not take MULTAQ if you have symptoms of heart failure that recently worsened and you were hospitalized, or if you have severe heart failure.
    Call your healthcare provider right away if you develop any of the following signs or symptoms of heart failure during treatment with MULTAQ:
    - shortness of breath or wheezing at rest
    - wheezing, chest tightness or coughing up frothy sputum at rest, nighttime or after minor exercise
    - trouble sleeping or waking up at night because of breathing problems
    - using more pillows to prop yourself up at night so you can breathe more easily
    - gaining more than 5 pounds quickly
    - increasing swelling of feet or legs
  - A certain type of irregular heartbeat (rhythm) called permanent atrial fibrillation (AF). Permanent AF is when you and your healthcare provider decide not to try to change your heart rhythm back to a normal heart rhythm or your heart rhythm cannot be changed back to a normal rhythm.
    Do not take MULTAQ if you have permanent AF. Your healthcare provider should check your heart rhythm regularly to make sure your heart keeps a normal rhythm.
    Call your healthcare provider right away if you develop any of the following signs or symptoms of AF during treatment with MULTAQ such as:

- fast or irregular heartbeat or pulse
- chest pain
- dizziness or lightheadedness

- tiredness or weakness
- reduced ability to exercise
- shortness of breath

MULTAQ doubles your risk of dying if you have these conditions. Your healthcare provider may give you a medicine to help prevent blood clots and decrease your risk of stroke during treatment with MULTAQ. Tell your healthcare provider right away if you develop any of the following signs or symptoms of stroke during treatment with MULTAQ such as:

- numbness or weakness in the face, arms, or legs, especially on 1 side of the body
- confusion, trouble speaking, or difficulty understanding things
- trouble seeing in 1 or both eyes
- trouble walking, dizziness, loss of balance, or lack of coordination

- Liver problems. MULTAQ may cause severe liver problems, including life-threatening liver failure.
  Do not take MULTAQ if you have severe liver problems. Your healthcare provider may order blood tests to check your liver before you start taking MULTAQ and during treatment.
  Call your healthcare provider right away if you develop any of the following signs and symptoms of liver problems during treatment with MULTAQ:

- loss of appetite, nausea, vomiting
- fever, feeling unwell, unusual tiredness
- itching

- yellowing of the skin or the whites of the eyes (jaundice)
- unusual darkening of the urine
- right upper stomach area pain or discomfort

What is MULTAQ?
MULTAQ is a prescription medicine used to lower the chance of hospitalization for atrial fibrillation (AF) in people who currently have a normal heart rhythm and have had certain types of AF (paroxysmal or persistent AF) in the past.
It is not known if MULTAQ is safe and effective in children younger than age 18 years old.

Who should not take MULTAQ?
See "What is the most important information I should know about taking MULTAQ?"
Do not take MULTAQ if:

- you have a certain type of heart problem called heart block, and you do not have an implanted pacemaker
- your heart rate is less than 50 beats each minute
- you have had liver or lung problems after using amiodarone
- you have a certain type of electrocardiogram (ECG) abnormality including QTc or PR interval prolongation
- you take certain medicines that can change the amount of MULTAQ that gets into your body such as:

- nefazodone
- ritonavir
- ketoconazole
- itraconazole
- erythromycin

- voriconazole
- telithromycin
- clarithromycin
- cyclosporin

- you take certain medicines that can lead to a dangerous abnormal heart rhythm such as:

- phenothiazines
- tricyclic antidepressants

- macrolide antibiotics
- certain medicines for abnormal heart rhythm or fast heartbeat (Class I and III antiarrhythmics)

- you are allergic to dronedarone or any of the other ingredients in MULTAQ. See the end of this Medication Guide for a complete list of ingredients in MULTAQ.

What should I tell my healthcare provider before taking MULTAQ?
Before taking MULTAQ, tell your healthcare provider about all of your medical conditions, including if you:

- have any other heart problems, including heart rhythm problems, or have had a stroke
- have an implanted pacemaker
- have liver or kidney problems
- have lung problems
- have low levels of potassium or magnesium in your blood
- are pregnant or plan to become pregnant. MULTAQ may harm your unborn baby.
  Females who can become pregnant
  - Your healthcare provider will do a pregnancy test before you start treatment with MULTAQ.
  - Use effective birth control (contraception) during treatment and for 5 days after your final dose of MULTAQ.
  - Tell your healthcare provider right away if you think you are pregnant or become pregnant during treatment with MULTAQ.
- are breastfeeding or plan to breastfeed. It is not known if MULTAQ passes into your breast milk. Do not breastfeed during treatment and for 5 days after the final dose of MULTAQ.

Tell your healthcare provider about all the medicines you take, including prescription and over-the-counter medicines, vitamins, and herbal supplements. Taking MULTAQ with certain other medicines may affect the amount of MULTAQ or other medicines in your blood and may increase your risk of side effects or affect how well MULTAQ or the other medicines work.
Especially tell your healthcare provider if you take:

- medicine for high blood pressure, chest pain, or other heart conditions
- statin medicine to lower blood cholesterol
- medicine for tuberculosis (TB)
- medicine for seizures
- digoxin
- warfarin or other blood thinner medicines
- medicine for organ transplant
- an herbal supplement called St. John's wort
- water pills (diuretics)

Know the medicines you take. Keep a list of them to show to your healthcare provider and pharmacist when you get a new medicine.

How should I take MULTAQ?

- Take MULTAQ exactly as your healthcare provider tells you.
- Take MULTAQ 2 times a day, in the morning and evening with a meal.
- Do not stop taking MULTAQ without first talking to your healthcare provider.
- If you miss a dose of MULTAQ, skip the missed dose and take your next dose at your regular time. Do not take 2 doses at the same time to make up for a missed dose.
- If you take too much MULTAQ, call your healthcare provider or go to the nearest hospital emergency room right away.

What should I avoid while taking MULTAQ?
Do not drink grapefruit juice during treatment with MULTAQ. Grapefruit juice can increase the amount of MULTAQ in your blood and can increase your chance of getting side effects.

What are the possible side effects of MULTAQ?
MULTAQ may cause serious side effects, including:

- See "What is the most important information I should know about MULTAQ?"
- Inflammation of the lungs, including scarring and thickening. Call your healthcare provider if you develop shortness of breath or a dry cough during treatment with MULTAQ.
- Low potassium and magnesium levels in your blood. This can happen if you take certain water pills (diuretics) during treatment with MULTAQ. Your healthcare provider may check you for this problem before and during treatment. Tell your healthcare provider if you develop any of the following symptoms of low potassium or low magnesium during treatment with MULTAQ:

- nausea or vomiting
- weakness or sleepiness
- muscle weakness, spasms, or tremors
- loss of appetite

- constipation
- heart palpitations
- tingling or numbness

- Changes in the electrical activity in your heart called QT interval prolongation. QT interval prolongation can increase your chance of getting dangerous abnormal heart rhythms.
- Kidney problems and kidney failure. MULTAQ can cause changes in kidney function that can be serious and lead to kidney failure, especially in people with heart failure or people with low body fluid levels. Your healthcare provider will check your blood for signs of kidney problems during treatment. Tell your healthcare provider if you develop any of the following symptoms of kidney problems during treatment with MULTAQ:

- loss of appetite
- nausea and vomiting
- muscle cramps
- dry, itchy skin

- swelling of the feet and ankles
- shortness of breath
- trouble sleeping
- urinating too much or too little

The most common side effects of MULTAQ include:

- diarrhea
- weakness, lack of energy, and feeling very tired or sleepy (asthenia)
- nausea
- skin problems such as redness, rash, and itching

- stomach area (abdominal) pain
- slow heart rate (bradycardia)
- vomiting
- indigestion

Your healthcare provider may stop treatment with MULTAQ if you develop certain side effects. These are not all of the possible side effects of MULTAQ.
Call your doctor for medical advice about side effects. You may report side effects to FDA at 1-800-FDA-1088.

How should I store MULTAQ?
Store MULTAQ at room temperature between 68°F to 77°F (20°C to 25°C).
Keep MULTAQ and all medicines out of the reach of children.

General information about the safe and effective use of MULTAQ.
Medicines are sometimes prescribed for purposes other than those listed in a Medication Guide. Do not use MULTAQ for a condition for which it was not prescribed. Do not give MULTAQ to other people, even if they have the same symptoms or condition. It may harm them. You can ask your pharmacist or healthcare provider for information about MULTAQ that is written for health professionals.

What are the ingredients in MULTAQ?
Active ingredient: dronedarone
Inactive ingredients:
tablet core: Colloidal silicon dioxide, crospovidone, hypromellose, lactose monohydrate, magnesium stearate, poloxamer 407, starch.
tablet coating: Carnauba wax, hypromellose, polyethylene glycol 6000, titanium dioxide.
Manufactured by:
sanofi-aventis U.S. LLC
Morristown, NJ 07960
A SANOFI COMPANY
©sanofi-aventis 2025
All rights reserved.
MULTAQ is a registered trademark of sanofi-aventis.
For more information go to www.sanofi-aventis.us or call sanofi-aventis Medical Information Services at 1-800-633-1610 option 1.

Distributed By:

Cardinal Health

Dublin, OH 43017

ER7605 Rev. C

This Medication Guide has been approved by the U.S. Food and Drug Administration.
Revised May 2025

Package/Label Display Panel

Contains Approximately

1260 Tablets

MULTAQ®

(dronedarone) Tablets

400 mg

Each tablet contains:

dronedarone hydrochloride equivalent to

400mg dronedarone.

Dispense with Medication Guide.

Rx Only

WARNING: Keep out of reach of

children.